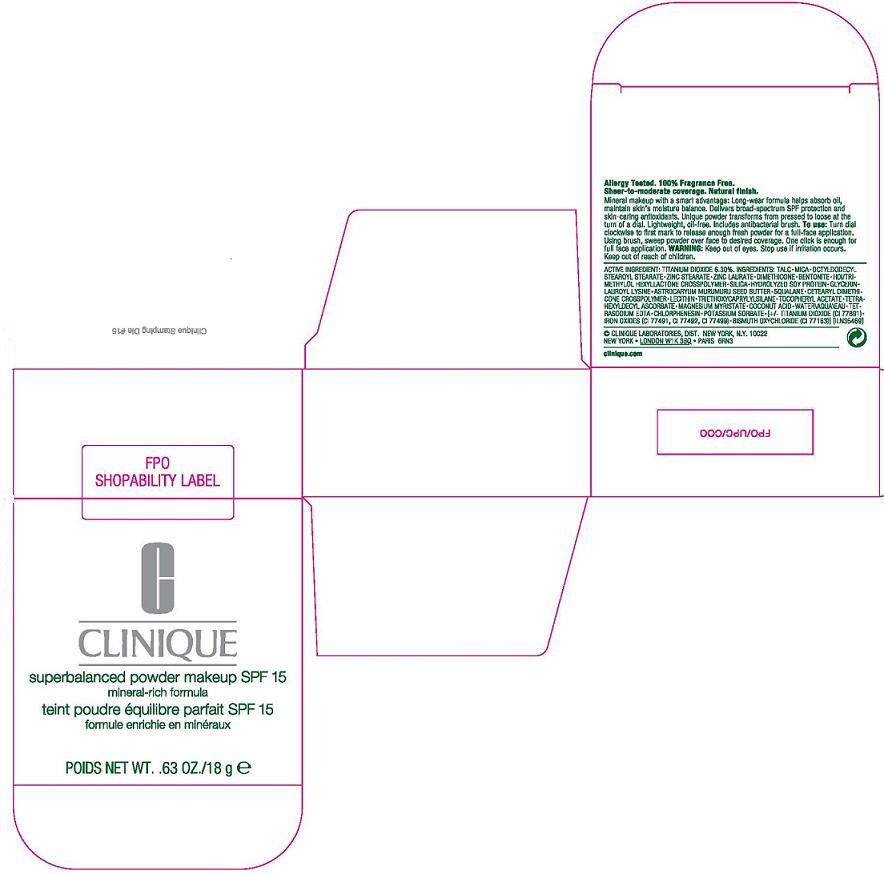 DRUG LABEL: SUPERBALANCED
NDC: 49527-746 | Form: POWDER
Manufacturer: CLINIQUE  LABORATORIES INC.
Category: otc | Type: HUMAN OTC DRUG LABEL
Date: 20110913

ACTIVE INGREDIENTS: TITANIUM DIOXIDE 6.3 g/100 g
INACTIVE INGREDIENTS: TALC; MICA; OCTYLDODECYL STEAROYL STEARATE; ZINC STEARATE; ZINC LAURATE; DIMETHICONE; BENTONITE; SILICON DIOXIDE; GLYCERIN; LAUROYL LYSINE; ASTROCARYUM MURUMURU SEED BUTTER; SQUALANE; LECITHIN, SOYBEAN; TRIETHOXYCAPRYLYLSILANE; ALPHA-TOCOPHEROL ACETATE; TETRAHEXYLDECYL ASCORBATE; MAGNESIUM MYRISTATE; COCONUT ACID; WATER; EDETATE SODIUM; CHLORPHENESIN; POTASSIUM SORBATE; FERRIC OXIDE RED; BISMUTH OXYCHLORIDE

active ingredient: titanium dioxide 6.30%

INACTIVE INGREDIENT

inactive ingredients: talc [] mica [] octyldodecyl stearoyl stearate [] zinc stearate [] zinc laurate [] dimethicone [] bentonite [] hdi/trimethylol hexyllactone crosspolymer [] silica [] hydrolyzed soy protein [] glycerin [] lauroyl lysine [] astrocaryum murumuru seed butter [] squalane [] cetearyl dimethicone crosspolymer [] lecithin [] triethoxycaprylylsilane [] tocopheryl acetate [] tetrahexyldecyl ascorbate [] magnesium myristate [] coconut acid [] water\aqua\eau [] tetrasodium edta [] chlorphenesin [] potassium sorbate [] [+/- titanium dioxide (ci 77891) [] iron oxides (ci 77491, ci 77492, ci 77499) [] bismuth oxychloride (ci 77163)

WARNINGS AND PRECAUTIONS

warning: keep out of eyes. stop use if irritation occurs. keep out of reach of children.

PACKAGE LABEL

clinique
superbalanced powder makeup
spf 15
mineral-rich formula
net wt. 0.63 oz/ 18g
clinique laboratories distr.
new york, ny 10022